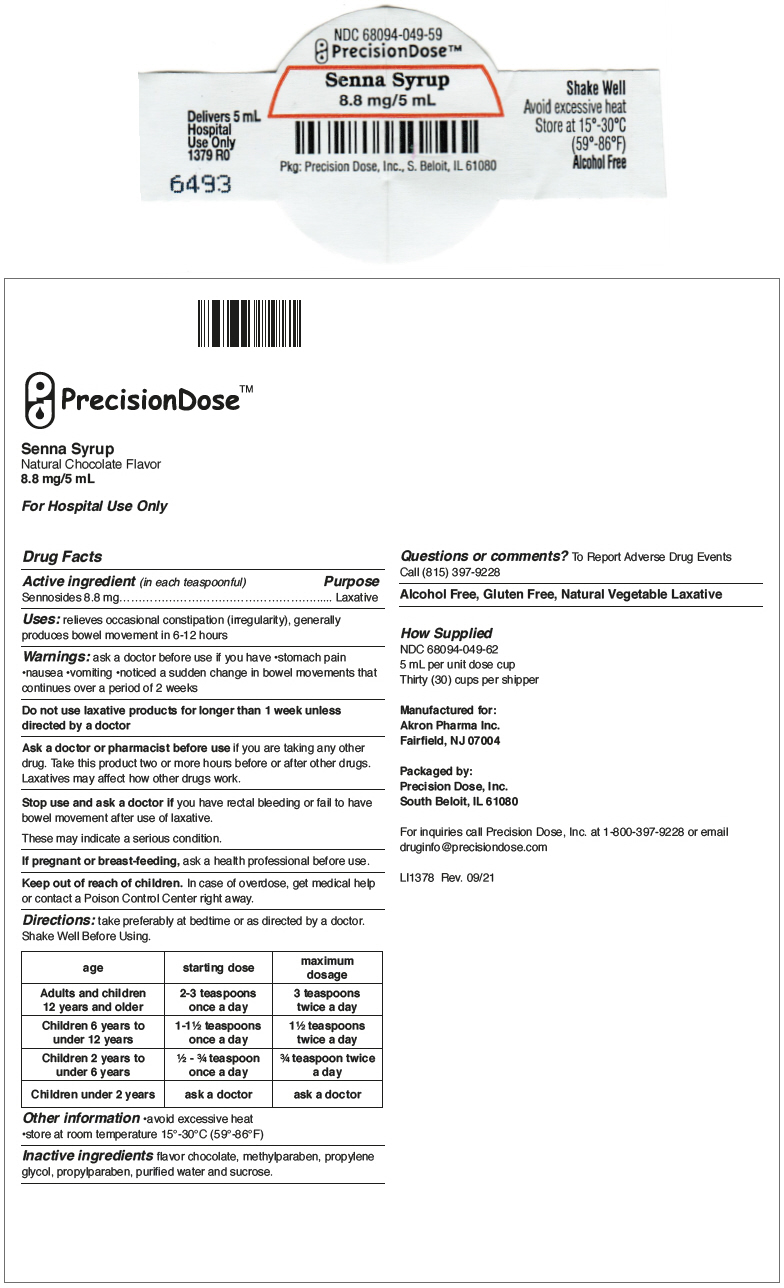 DRUG LABEL: SENNA
NDC: 68094-049 | Form: SYRUP
Manufacturer: Precision Dose, Inc.
Category: otc | Type: HUMAN OTC DRUG LABEL
Date: 20240705

ACTIVE INGREDIENTS: Sennosides A and B 417.12 mg/237 mL
INACTIVE INGREDIENTS: Methylparaben; PROPYLENE GLYCOL; PROPYLPARABEN; WATER; SUCROSE

Onelax Senna
Senna Syrup

Senna Syrup
Natural Chocolate Flavor
8.8 mg/5 mL

For Hospital Use Only

Drug Facts

Active ingredient (in each teaspoonful)

Sennosides 8.8 mg

Purpose

Laxative

Uses

relieves occasional constipation (irregularity), generally produces bowel movement in 6-12 hours

Warnings

ask a doctor before use if you have

- stomach pain
- nausea
- vomiting
- noticed a sudden change in bowel movements that continues over a period of 2 weeks

Do not use laxative products for longer than 1 week unless directed by a doctor

Ask a doctor or pharmacist before use if you are taking any other drug. Take this product two or more hours before or after other drugs. Laxatives may affect how other drugs work.

Stop use and ask a doctor if you have rectal bleeding or fail to have bowel movement after use of laxative.

These may indicate a serious condition.

PREGNANCY OR BREAST FEEDING

If pregnant or breast-feeding, ask a health professional before use.

Keep out of reach of children. In case of overdose, get medical help or contact a Poison Control Center right away.

Directions

take preferably at bedtime or as directed by a doctor. Shake Well Before Using.

age | starting dose | maximum dosage
Adults and children 12 years and older | 2-3 teaspoons once a day | 3 teaspoons twice a day
Children 6 years to under 12 years | 1-1½ teaspoons once a day | 1½ teaspoons twice a day
Children 2 years to under 6 years | ½ - ¾ teaspoon once a day | ¾ teaspoon twice a day
Children under 2 years | ask a doctor | ask a doctor

Other information

- avoid excessive heat
- store at room temperature 15°-30°C (59°-86°F)

Inactive ingredients

flavor chocolate, methylparaben, propylene glycol, propylparaben, purified water and sucrose.

Questions or comments?

To Report Adverse Drug Events Call (815) 397-9228

Alcohol Free, Gluten Free, Natural Vegetable Laxative

How Supplied

NDC 68094-049-62
5 mL per unit dose cup
Thirty (30) cups per shipper

Manufactured for:
Akron Pharma Inc.
Fairfield, NJ 07004

Packaged by:
Precision Dose, Inc.
South Beloit, IL 61080

For inquiries call Precision Dose, Inc. at 1-800-397-9228 or email druginfo@precisiondose.com

LI1378 Rev. 09/21

PRINCIPAL DISPLAY PANEL - 5 mL Cup Label

NDC 68094-049-59
PrecisionDose™

Senna Syrup
8.8 mg/5 mL

Pkg: Precision Dose, Inc., S. Beloit, IL 61080